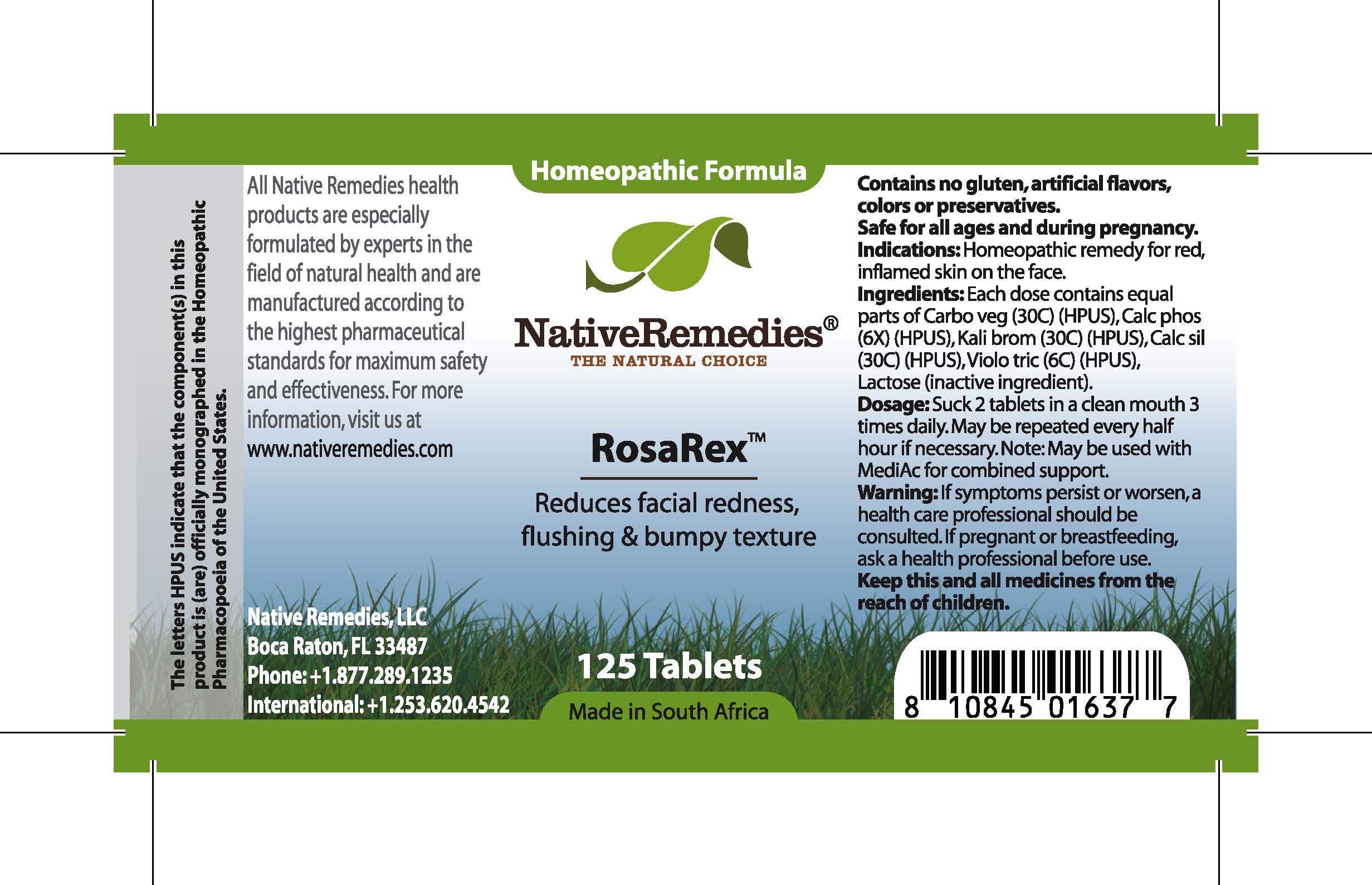 DRUG LABEL: RosaRex
NDC: 68647-118 | Form: TABLET
Manufacturer: Feelgood Health
Category: homeopathic | Type: HUMAN OTC DRUG LABEL
Date: 20100719

ACTIVE INGREDIENTS: ACTIVATED CHARCOAL 30 [hp_C]/1 1; TRIBASIC CALCIUM PHOSPHATE 6 [hp_X]/1 1; POTASSIUM BROMIDE 30 [hp_C]/1 1; CALCIUM SILICATE 30 [hp_C]/1 1; VIOLA TRICOLOR 6 [hp_C]/1 1
INACTIVE INGREDIENTS: LACTOSE

ROSAREX

DESCRIPTION

Reduces facial redness, flushing and bumpy texture

INDICATIONS AND USAGE

Indications: Homeopathic remedy for red, inflamed skin on the face.

DOSAGE AND ADMINISTRATION

Dosage: Dissolve 2 tablets in a clean mouth 3 times daily. May be repeated every half hour if necessary. May be used with MediAc™ for combined support.

GENERAL PRECAUTIONS

Caution: If symptoms persist or worsen, a health care professional should be consulted. If pregnant or breastfeeding, ask a health professional before use. Keep this and all medicines from the reach of children.

ACTIVE INGREDIENT

Ingredients: Each dose contains equal parts of Carbo veg (30C) (HPUS), Calc phos (6X) (HPUS), Kali brom (30C) (HPUS), Calc sil (30C) (HPUS), Violo tric (6C) (HPUS)

Lactose (inactive ingredient).

PREGNANCY

If pregnant or breastfeeding, ask a health professional before use.

USER SAFETY WARNINGS

Contains no gluten, artificial flavors, colors or preservatives. Safe for all ages and during pregnancy.

PATIENT COUNSELING INFORMATION

All Native Remedies health products are especially formulated by experts in the field of natural health and are manufactured according to the highest pharmaceutical standards for maximum safety and effectiveness. For more information, visit us at www.nativeremedies.com

Distributed by

Native Remedies, LLC

6531 Park of Commerce Blvd.

Suite 160

Boca Raton, FL 33487

Phone: 1.877.289.1235

International: + 1.561.999.8857

The letters HPUS indicate that the component(s) in this product is (are) officially monographed in the Homeopathic Pharmacopoeia of the United States.